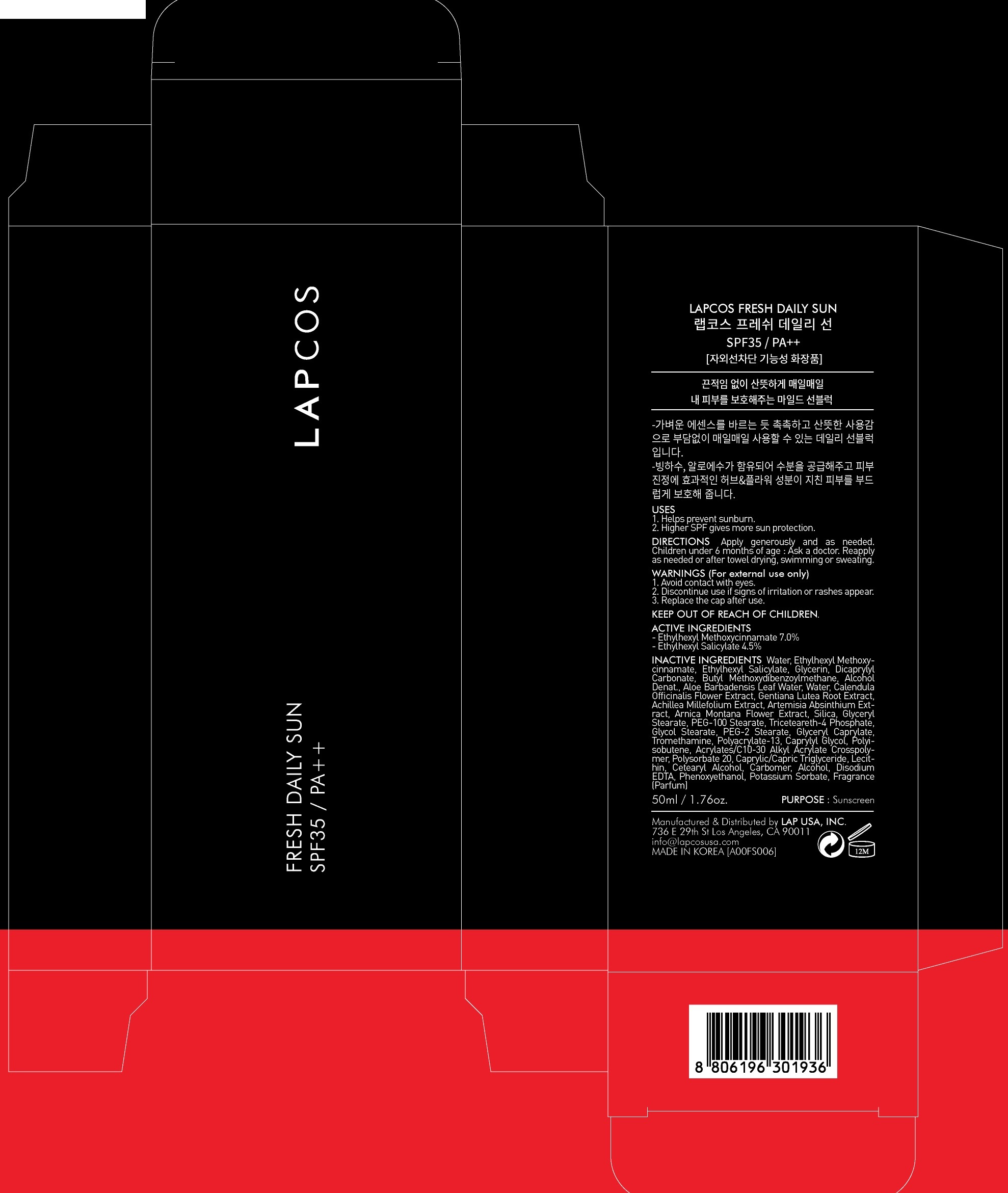 DRUG LABEL: LAPCOS Fresh Daily Sun
NDC: 71379-010 | Form: CREAM
Manufacturer: LAP CO.,LTD
Category: otc | Type: HUMAN OTC DRUG LABEL
Date: 20170504

ACTIVE INGREDIENTS: Octinoxate 3.50 g/50 mL; Octisalate 2.25 g/50 mL
INACTIVE INGREDIENTS: Water; Glycerin

ACTIVE INGREDIENT

Active ingredients: Ethylhexyl Methoxycinnamate 7.0%, Ethylhexyl Salicylate 4.5%

INACTIVE INGREDIENT

Inactive ingredients: Water,Glycerin,Dicaprylyl Carbonate,Butyl Methoxydibenzoylmethane,Alcohol Denat.,Aloe Barbadensis Leaf Water,Water,Calendula Officinalis Flower Extract,Gentiana Lutea Root Extract,Achillea Millefolium Extract,Artemisia Absinthium Extract,Arnica Montana Flower Extract,Silica,Glyceryl Stearate,PEG-100 Stearate,Triceteareth-4 Phosphate,Glycol Stearate,PEG-2 Stearate,Glyceryl Caprylate,Tromethamine,Polyacrylate-13,Caprylyl Glycol,Polyisobutene,Acrylates/C10-30 Alkyl Acrylate Crosspolymer,Polysorbate 20,Caprylic/Capric Triglyceride,Lecithin,Cetearyl Alcohol,Carbomer,Alcohol,Disodium EDTA,Phenoxyethanol,Potassium Sorbate,Fragrance(Parfum)

PURPOSE

Purpose: Sunscreen

WARNINGS

Warnings: For external use only Avoid contact with eyes. Discontinue use if signs of irritation or rashes appear. Replace the cap after use. Keep Out of Reach of Children

DESCRIPTION

Uses: - Helps prevent sunburn - Higher SPF gives more sun protection

Directions: - Apply generously and as needed. - Children under 6 months of age : Ask a doctor. - Reapply as needed or after towel drying, swimming or sweating.